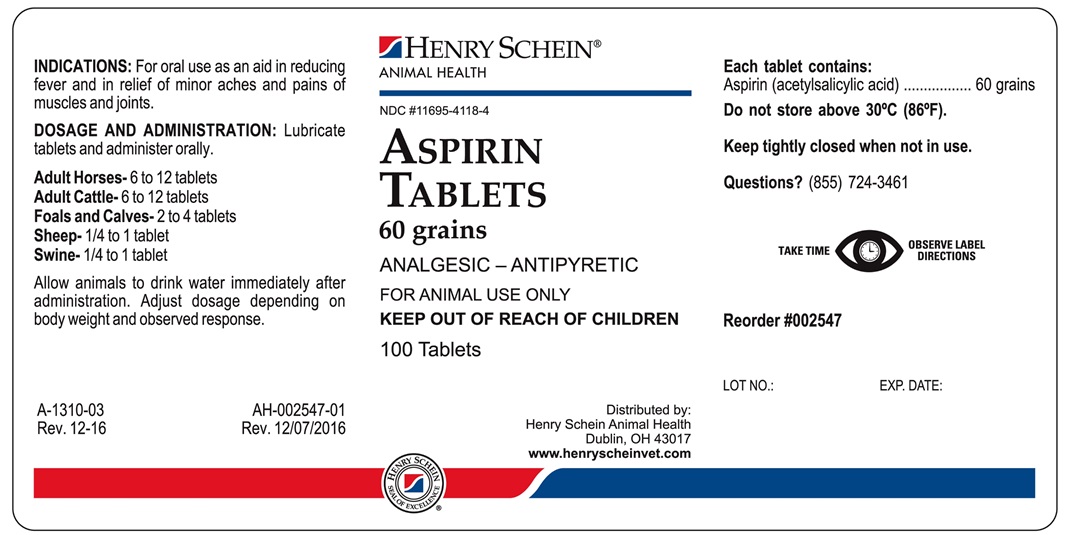 DRUG LABEL: ASPIRIN
NDC: 11695-4118 | Form: TABLET
Manufacturer: Butler Animal Health Supply dba Henry Schein Animal Health
Category: animal | Type: OTC ANIMAL DRUG LABEL
Date: 20180430

ACTIVE INGREDIENTS: ASPIRIN 3.9 g/1 1

ASPIRIN TABLETS

INDICATIONS AND USAGE

60 grains

ANALGESIC - ANTIPYRETIC

FOR ANIMAL USE ONLY

KEEP OUT OF REACH OF CHILDREN

INDICATIONS

For oral use in reducing fever and as an aid in the temporary relief of minor aches and pains of muscles and joints.

DOSAGE AND ADMINISTRATION

Lubricate tablets and administer orally.

Adult Horses-3 to 6 tablets
Adult Cattle-8 to 12 tablets
Foals and Calves-1 to 2 tablets
Sheep-1/2 to 1 tablet
Swine-1/4 to 1/2 tablet

Allow animals to drink water immediately after administration. Adjust dosage depending on body weight and observed response. Dosage may be repeated at 12-hour intervals if necessary.

Each tablet contains

Acetylsalicylic Acid
(Aspirin)................................60 grains

STORAGE AND HANDLING

Do not store above 30°C (86°F).
Keep tightly closed when not in use.
TAKE TIME OBSERVE LABEL DIRECTIONS